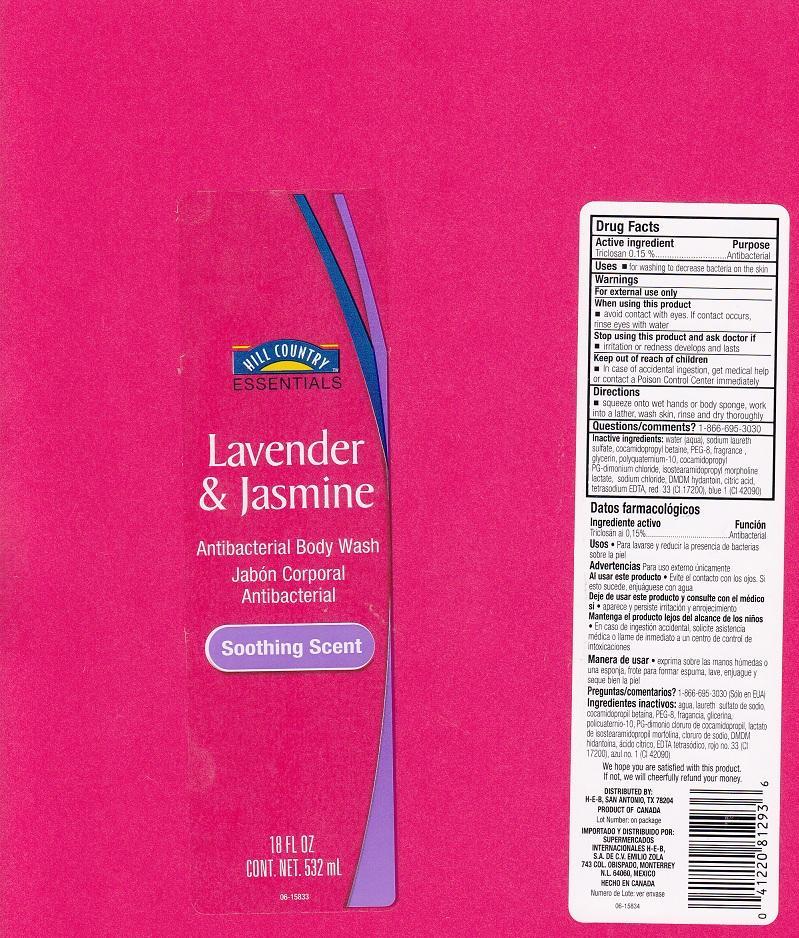 DRUG LABEL: HILL COUNTRY ESSENTIALS
NDC: 37808-806 | Form: LIQUID
Manufacturer: HEB
Category: otc | Type: HUMAN OTC DRUG LABEL
Date: 20130405

ACTIVE INGREDIENTS: TRICLOSAN 1.5 mg/1 mL
INACTIVE INGREDIENTS: WATER; SODIUM LAURETH SULFATE; COCAMIDOPROPYL BETAINE; POLYETHYLENE GLYCOL 400; GLYCERIN; POLYQUATERNIUM-10 (400 CPS AT 2%); COCAMIDOPROPYL PG-DIMONIUM CHLORIDE; ISOSTEARAMIDOPROPYL MORPHOLINE LACTATE; SODIUM CHLORIDE; DMDM HYDANTOIN; CITRIC ACID MONOHYDRATE; EDETATE SODIUM; D&C RED NO. 33; FD&C BLUE NO. 1

DRUG FACTS

ACTIVE INGREDIENT

TRICLOSAN 0.15%

PURPOSE

ANTIBACTERIAL

USES

FOR WASHING TO DECREASE BACTERIA ON THE SKIN.

WARNINGS

FOR EXTERNAL USE ONLY.

WHEN USING THIS PRODUCT

AVOID CONTACT WITH EYES. IF CONTACT OCCURS, RINSE EYES WITH WATER.

STOP USING THIS PRODUCT AND ASK DOCTOR IF

IRRITATION OR REDNESS DEVELOPS AND LASTS.

KEEP OUT OF REACH OF CHILDREN

IN CASE OF ACCIDENTAL INGESTION, GET MEDICAL HELP OR CONTACT A POISON CONTROL CENTER IMMEDIATELY.

DIRECTIONS

SQUEEZE ONTO WET HANDS OR BODY SPONGE, WORK INTO A LATHER, WASH SKIN, RINSE AND DRY THOROUGHLY.

QUESTIONS/COMMENTS?

1-866-695-3030

INACTIVE INGREDIENTS:

WATER (AQUA), SODIUM LAURETH SULFATE, COCAMIDOPROPYL BETAINE, PEG-8, FRAGRANCE, GLYCERIN, POLYQUATERNIUM-10, COCAMIDOPROPYL PG-DIMONIUM CHLORIDE, ISOSTEARAMIDOPROPYL MORPHOLINE LACTATE, SODIUM CHLORIDE, DMDM HYDANTOIN, CITRIC ACID, TETRASODIUM EDTA, RED 33 (CI 17200), BLUE 1 (CI 42090).